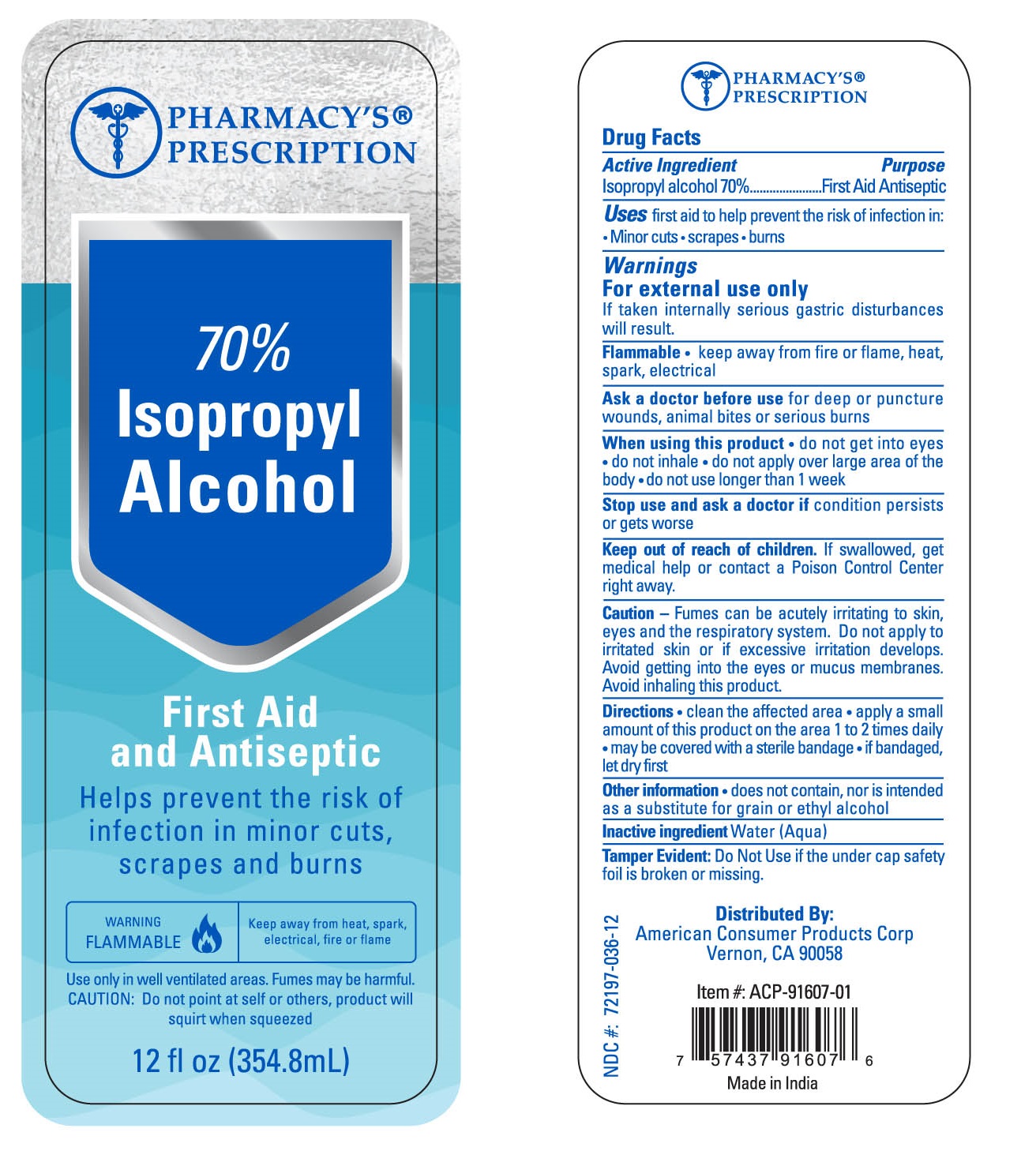 DRUG LABEL: Pharmacys Prescription IPA
NDC: 72197-036 | Form: LIQUID
Manufacturer: American Consumer Products Corp
Category: otc | Type: HUMAN OTC DRUG LABEL
Date: 20200914

ACTIVE INGREDIENTS: ISOPROPYL ALCOHOL 70 mL/100 mL
INACTIVE INGREDIENTS: WATER

Pharmacys Prescription 70% Isopropyl Alcohol

Active Ingredient (by volume)

Isopropyl alcohol (70% conc.)

Purpose

First Aid Antiseptic

Uses

Uses: first aid to help prevent the risk of infection in minor cuts, scrapes, burns

Warnings

For external use only

If taken internally serious gastric disturbances will result

Flammable • keep away from fire or flame, heat, spark, electrical

When using this product • do not get into eyes • do not inhale • do not apply over large area of the body • do not use longer than 1 week

Stop use

Stop use and ask a doctor if condition persists or gets worse

Keep out of reach of children. If swallowed, get medical help or contact a Poison Control Center right away.

Caution

Caution - Fumes can be acutely irritating to skin, eyes and the respiratory system. Do not apply to irritated skin or if excessive irritation develops. Avoid getting into eyes or mucus membranes. Avoid inhaling this product.

Directions

Directions • clean the affected area • apply a small amount of this product on the area 1 to 2 times daily • may be covered with a sterile bandage • if bandaged, let dry first

Other information

Other information • does not contain, nor is intended as a substitute for grain or ethyl alcohol.

Inactive ingredient

Inactive ingredient Water (Aqua)

Tamper Evident

Tamper Evident: Do Not Use if the under cap safety foil is broken or missing.

Distributed by

American Consumer Products Corp

Vernon, CA 90058